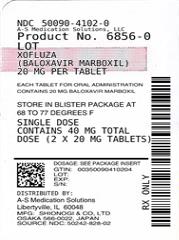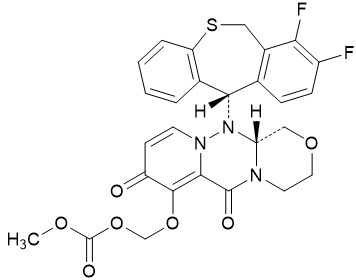 DRUG LABEL: Xofluza
NDC: 50090-4102 | Form: TABLET, FILM COATED
Manufacturer: A-S Medication Solutions
Category: prescription | Type: HUMAN PRESCRIPTION DRUG LABEL
Date: 20210416

ACTIVE INGREDIENTS: BALOXAVIR MARBOXIL 20 mg/1 1
INACTIVE INGREDIENTS: LACTOSE MONOHYDRATE; CROSCARMELLOSE SODIUM; POVIDONE K25; MICROCRYSTALLINE CELLULOSE; SODIUM STEARYL FUMARATE; TITANIUM DIOXIDE; HYPROMELLOSE, UNSPECIFIED; TALC

HIGHLIGHTS OF PRESCRIBING INFORMATION

These highlights do not include all the information needed to use XOFLUZA safely and effectively. See full prescribing information for XOFLUZA.
XOFLUZA® (baloxavir marboxil) tablets, for oral use
XOFLUZA® (baloxavir marboxil) for oral suspension
Initial U.S. Approval: 2018

RECENT MAJOR CHANGES

Indications and Usage
Post-Exposure Prophylaxis of Influenza (1.2) | 11/2020
Dosage and Administration (2.1, 2.2, 2.3) | 3/2021

1 INDICATIONS AND USAGE

XOFLUZA is an influenza virus polymerase acidic (PA) endonuclease inhibitor indicated for:

- Treatment of acute uncomplicated influenza in patients 12 years of age and older who have been symptomatic for no more than 48 hours and who are:
  - otherwise healthy, or
  - at high risk of developing influenza-related complications. (1.1)
- Post-exposure prophylaxis of influenza in patients 12 years of age and older following contact with an individual who has influenza. (1.2)

Limitations of Use

Influenza viruses change over time, and factors such as the virus type or subtype, emergence of resistance, or changes in viral virulence could diminish the clinical benefit of antiviral drugs. Consider available information on drug susceptibility patterns for circulating influenza virus strains when deciding whether to use XOFLUZA. (1.3)

2 DOSAGE AND ADMINISTRATION

Treatment and Post-Exposure Prophylaxis of Influenza

XOFLUZA should be taken as a single dose as soon as possible and within 48 hours of influenza symptom onset for treatment of acute uncomplicated influenza or following contact with an individual who has influenza. XOFLUZA should be taken with or without food. (2.1, 2.2)

Patient Body Weight (kg) | Recommended Single Oral Dose in Patients 12 Years of Age and Older
Less than 80 kg | One 40 mg tablet (blister card contains one 40 mg tablet)
At least 80 kg | One 80 mg tablet (blister card contains one 80 mg tablet)

Refer to the Full Prescribing Information for information on recommended dosage of XOFLUZA oral suspension in adults and adolescents (12 years of age and older). (2.2)

Refer to the Full Prescribing Information for additional information on preparation of XOFLUZA for oral suspension for oral or enteral use. (2.3)

3 DOSAGE FORMS AND STRENGTHS

- Tablets: 40 mg and 80 mg. (3)
- For oral suspension: 40 mg/20 mL when constituted for final concentration of 2 mg/mL. (3)

4 CONTRAINDICATIONS

XOFLUZA is contraindicated in patients with a history of hypersensitivity to baloxavir marboxil or any of its ingredients. (4)

5 WARNINGS AND PRECAUTIONS

- Hypersensitivity such as anaphylaxis, angioedema, urticaria, and erythema multiforme: Initiate appropriate treatment if an allergic-like reaction occurs or is suspected. (5.1)
- Risk of bacterial infection: Serious bacterial infections may begin with influenza-like symptoms or may coexist with, or occur as, a complication of influenza. XOFLUZA has not been shown to prevent such complications. Prescribers should be alert to potential secondary bacterial infections and treat them as appropriate. (5.2)

6 ADVERSE REACTIONS

Adverse events reported in at least 1% of adult and adolescent influenza subjects treated with XOFLUZA included diarrhea (3%), bronchitis (3%), nausea (2%), sinusitis (2%), and headache (1%). (6.1)

To report SUSPECTED ADVERSE REACTIONS, contact Genentech at 1-888-835-2555 or FDA at 1-800-FDA-1088 or www.fda.gov/medwatch.

7 DRUG INTERACTIONS

- Avoid coadministration of XOFLUZA with dairy products, calcium-fortified beverages, polyvalent cation-containing laxatives, antacids, or oral supplements (e.g., calcium, iron, magnesium, selenium, or zinc). (2.1, 7.1)
- Live attenuated influenza vaccines may be affected by antivirals. (7.2)

FULL PRESCRIBING INFORMATION

1 INDICATIONS AND USAGE

1.1 Treatment of Influenza

XOFLUZA is indicated for the treatment of acute uncomplicated influenza in patients 12 years of age and older who have been symptomatic for no more than 48 hours and who are:

- otherwise healthy, or
- at high risk of developing influenza-related complications^1 [see Clinical Studies (14.2)].

1.2 Post-Exposure Prophylaxis of Influenza

XOFLUZA is indicated for post-exposure prophylaxis of influenza in persons 12 years of age and older following contact with an individual who has influenza [see Clinical Studies (14.3)].

1.3 Limitations of Use

Influenza viruses change over time, and factors such as the virus type or subtype, emergence of resistance, or changes in viral virulence could diminish the clinical benefit of antiviral drugs. Consider available information on drug susceptibility patterns for circulating influenza virus strains when deciding whether to use XOFLUZA [see Microbiology (12.4) and Clinical Studies (14)].

2 DOSAGE AND ADMINISTRATION

2.1 Dosage and Administration Overview

XOFLUZA is available in two dosage forms:

- XOFLUZA tablets
- XOFLUZA for oral suspension. This granule formulation is intended for patients who are unable to or have difficulty swallowing tablets, or those who require enteral administration [see Dosage and Administration (2.3)].

XOFLUZA should be taken as soon as possible after influenza symptom onset or exposure to influenza and may be taken with or without food. However, coadministration of XOFLUZA with dairy products, calcium-fortified beverages, polyvalent cation-containing laxatives, antacids, or oral supplements (e.g., calcium, iron, magnesium, selenium, or zinc) should be avoided [see Drug Interactions (7.1) and Clinical Pharmacology (12.3)].

2.2 Recommended Dosage

Treatment of Acute Uncomplicated Influenza or Post-Exposure Prophylaxis in Adults and Adolescents (12 Years of Age and Older)

XOFLUZA should be taken as a single dose as soon as possible and within 48 hours of influenza symptom onset for treatment of acute uncomplicated influenza or following contact with an individual who has influenza. The recommended dosage of XOFLUZA in patients 12 years of age or older is a single weight-based dose displayed in Tables 1 and 2.

Table 1 Recommended XOFLUZA Tablet Dosage in Adults and Adolescents (12 Years of Age and Older)
Patient Body Weight (kg) | Recommended Single Oral Dose (Tablets)
Less than 80 kg | One 40 mg tablet (blister card contains one 40 mg tablet)
At least 80 kg | One 80 mg tablet (blister card contains one 80 mg tablet)

Table 2 Recommended XOFLUZA Oral Suspension Dosage in Adults and Adolescents (12 Years of Age and Older)
Patient Body Weight (kg) | Recommended Single Oral Dose (Suspension)
Less than 80 kg | 40 mg/20 mL (1 bottle) taken as a single dose
At least 80 kg | 80 mg/40 mL (2 bottles) taken as a single dose

2.3 Preparation of XOFLUZA for Oral Suspension by Healthcare Provider

Prior to dispensing to the patient, constitute XOFLUZA for oral suspension with 20 mL of drinking water or sterile water. After constitution, each bottle of XOFLUZA suspension contains 40 mg of baloxavir marboxil per 20 mL of volume for a final concentration of 2 mg/mL. This dosage form can be used for oral or enteral use.

Constituting XOFLUZA for Oral Suspension

Prepare the suspension at the time of dispensing. Administration must occur within 10 hours after constitution because the product does not contain a preservative.

1. Gently tap the bottom of the bottle to loosen the granules.
2. Constitute XOFLUZA for oral suspension with 20 mL of drinking water or sterile water.
3. Gently swirl the suspension to ensure that the granules are evenly suspended. Do not shake.
4. Write the expiration time and date on the bottle label in the space provided (10 hours from constitution time).

Important Information for the Healthcare Provider

- Provide caregiver or patient with a measuring device (e.g., oral syringe, measuring cup) to deliver the prescribed dose of the suspension for oral use. For enteral administration (i.e., feeding tube), draw up suspension with an enteral syringe. Flush with 1 mL of water before and after enteral administration.
- Instruct the caregiver or patient that the total prescribed dose of XOFLUZA for oral suspension may require more than one bottle (e.g., for adults and adolescents weighing at least 80 kg).

3 DOSAGE FORMS AND STRENGTHS

XOFLUZA Tablets:

XOFLUZA 40 mg tablets are white to light yellow, oblong-shaped, film-coated tablets debossed with "BXM40" on one side.

XOFLUZA 80 mg tablets are white to light yellow, oblong shaped, film-coated tablets debossed with "BXM80" on one side.

XOFLUZA for Oral Suspension:

XOFLUZA for oral suspension contains 40 mg/20 mL or 2 mg/mL baloxavir marboxil after constitution with 20 mL of drinking water or sterile water. The granules are white to light yellow. The constituted product is a white to light yellow opaque suspension with strawberry flavor.

4 CONTRAINDICATIONS

XOFLUZA is contraindicated in patients with a history of hypersensitivity to baloxavir marboxil or any of its ingredients. Serious allergic reactions have included anaphylaxis, angioedema, urticaria, and erythema multiforme [see Warnings and Precautions (5.1)].

5 WARNINGS AND PRECAUTIONS

5.1 Hypersensitivity

Cases of anaphylaxis, urticaria, angioedema, and erythema multiforme have been reported in postmarketing experience with XOFLUZA. Appropriate treatment should be instituted if an allergic-like reaction occurs or is suspected. The use of XOFLUZA is contraindicated in patients with known hypersensitivity to XOFLUZA [see Contraindications (4) and Adverse Reactions (6.2)].

5.2 Risk of Bacterial Infections

There is no evidence of efficacy of XOFLUZA in any illness caused by pathogens other than influenza viruses. Serious bacterial infections may begin with influenza-like symptoms or may coexist with, or occur as, a complication of influenza. XOFLUZA has not been shown to prevent such complications. Prescribers should be alert to potential secondary bacterial infections and treat them as appropriate.

6 ADVERSE REACTIONS

6.1 Clinical Trials Experience

Because clinical trials are conducted under widely varying conditions, adverse reaction rates observed in the clinical trials of a drug cannot be directly compared to rates in the clinical trials of another drug and may not reflect the rates observed in practice.

The overall safety profile of XOFLUZA is based on data from 1,943 subjects 12 years of age and older in 4 controlled clinical trials who received XOFLUZA [see Clinical Studies (14)].

Treatment of Acute Uncomplicated Influenza

Adult and Adolescent Subjects:

The safety of XOFLUZA in adult and adolescent subjects is based on data from 3 placebo-controlled trials in which a total of 1,640 subjects received XOFLUZA: 1,334 (81%) subjects were 18 to 64 years of age, 209 (13%) subjects were adults 65 years of age or older, and 97 (6%) subjects were adolescents 12 to 17 years of age. These trials included otherwise healthy adults and adolescents (N=910) and subjects at high risk of developing complications associated with influenza (N=730). Of these, 1,440 subjects received XOFLUZA at the recommended dose [see Clinical Studies (14.1, 14.2)]. Trial 1 was a phase 2 dose-finding placebo-controlled trial where otherwise healthy adult subjects 20 to 64 years of age received single oral dose of XOFLUZA or placebo. Trial 2 was a placebo- and active-controlled trial in otherwise healthy adults and adolescents 12 to 64 years of age; subjects received weight-based XOFLUZA or placebo as a single oral dose on Day 1 or oseltamivir twice a day for 5 days. Trial 3 was a randomized, double-blind, placebo- and active-controlled trial where adults and adolescents at high risk of influenza complications 12 years of age and older received either XOFLUZA, placebo or oseltamivir.

Table 3 displays the most common adverse events (regardless of causality assessment) reported in at least 1% of adult and adolescent subjects who received XOFLUZA at the recommended dose in Trials 1, 2, and 3.

Table 3 Incidence of Adverse Events Occurring in at Least 1% of Adult and Adolescent Subjects Receiving XOFLUZA in the Acute Uncomplicated Influenza Trials 1, 2, and 3
Adverse Event | XOFLUZA (N=1,440) | Placebo (N=1,136)
Diarrhea | 3% | 4%
Bronchitis | 3% | 4%
Nausea | 2% | 3%
Sinusitis | 2% | 3%
Headache | 1% | 1%

Post-Exposure Prophylaxis of Influenza

The safety of XOFLUZA in adult and adolescent subjects is based on data from one placebo-controlled clinical trial in which 374 subjects, of which 303 were adult and adolescent subjects ≥ 12 years, received XOFLUZA: eight (3%) subjects were adults 65 years of age or older, and 12 (4%) subjects were adolescents 12 to 17 years of age. The most frequently reported AE in the total study population was nasopharyngitis which occurred in 6% of subjects who received XOFLUZA and 7% on placebo [see Clinical Studies (14.3)].

6.2 Postmarketing Experience

The following adverse reactions have been identified during postmarketing use of XOFLUZA. Because these reactions are reported voluntarily from a population of uncertain size, it is not possible to reliably estimate their frequency or establish a causal relationship to XOFLUZA exposure.

Immune System Disorders: Anaphylactic reactions, anaphylactic shock, anaphylactoid reactions, hypersensitivity reactions, angioedema (swelling of face, eyelids, tongue and lips)

Skin and Subcutaneous Tissue Disorders: Rash, urticaria, erythema multiforme

Gastrointestinal Disorders: Vomiting, hematochezia, melena, colitis

Psychiatric Disorders: Delirium, abnormal behavior, hallucinations

7 DRUG INTERACTIONS

7.1 Effect of Other Drugs on XOFLUZA

Baloxavir may form a chelate with polyvalent cations such as calcium, aluminum, or magnesium. Coadministration with polyvalent cation-containing products may decrease plasma concentrations of baloxavir [see Clinical Pharmacology (12.3)], which may reduce XOFLUZA efficacy. Avoid coadministration of XOFLUZA with dairy products, calcium-fortified beverages, polyvalent cation-containing laxatives, antacids, or oral supplements (e.g., calcium, iron, magnesium, selenium, or zinc).

7.2 Vaccines

The concurrent use of XOFLUZA with intranasal live attenuated influenza vaccine (LAIV) has not been evaluated. Concurrent administration of antiviral drugs may inhibit viral replication of LAIV and thereby decrease the effectiveness of LAIV vaccination. Interactions between inactivated influenza vaccines and XOFLUZA have not been evaluated.

8 USE IN SPECIFIC POPULATIONS

8.1 Pregnancy

Risk Summary

There are no adequate and well-controlled studies with XOFLUZA in pregnant women to inform a drug-associated risk of adverse developmental outcomes. There are risks to the mother and fetus associated with influenza virus infection in pregnancy [see Clinical Considerations]. In animal reproduction studies, no adverse developmental effects were observed in rats or rabbits with oral administration of baloxavir marboxil at exposures approximately 5 (rats) and 7 (rabbits) times the systemic baloxavir exposure at the maximum recommended human dose (MRHD) [see Data].

The estimated background risk of major birth defects and miscarriage for the indicated population is unknown. All pregnancies have a background risk of birth defects, loss, or other adverse outcomes. In the U.S. general population, the estimated background risk of major birth defects and miscarriage in clinically recognized pregnancies is 2%–4% and 15%–20%, respectively.

Clinical Considerations

Disease-Associated Maternal and/or Embryo/Fetal Risk

Pregnant women are at higher risk of severe complications from influenza, which may lead to adverse pregnancy and/or fetal outcomes, including maternal death, stillbirth, birth defects, preterm delivery, low birth weight, and small for gestational age.

Data

Animal Data

Baloxavir marboxil was administered orally to pregnant rats (20, 200, or 1,000 mg/kg/day from gestation day 6 to 17) and rabbits (30, 100, or 1,000 mg/kg/day from gestation day 7 to 19). No adverse embryo-fetal effects were observed in rats up to the highest dose of baloxavir marboxil (1,000 mg/kg/day), resulting in systemic baloxavir exposure (AUC) of approximately 5 times the exposure at the MRHD. In rabbits, fetal skeletal variations occurred at a maternally toxic dose (1,000 mg/kg/day) resulting in 2 abortions out of 19 pregnancies. No adverse maternal or embryo-fetal effects were observed in rabbits at the middle dose (100 mg/kg/day) resulting in systemic baloxavir exposure (AUC) approximately 7 times the exposure at the MRHD.

In the prenatal and postnatal development study in rats, baloxavir marboxil was administered orally at 20, 200, or 1,000 mg/kg/day from gestation day 6 to postpartum/lactation day 20. No significant effects were observed in the offspring at maternal systemic baloxavir exposure (AUC) approximately 5 times the exposure at the MRHD.

8.2 Lactation

Risk Summary

There are no data on the presence of baloxavir marboxil in human milk, the effects on the breastfed infant, or the effects on milk production. Baloxavir and its related metabolites were present in the milk of lactating rats [see Data]. The developmental and health benefits of breastfeeding should be considered along with the mother's clinical need for XOFLUZA and any potential adverse effects on the breastfed child from the drug or from the underlying maternal condition.

Data

In a lactation study, baloxavir and its related metabolites were excreted in the milk of lactating rats administered baloxavir marboxil (1 mg/kg) on postpartum/lactation day 11, with peak milk concentration approximately 5 times that of maternal plasma concentrations occurring 2 hours post-dose. No effects of baloxavir marboxil on growth and postnatal development were observed in nursing pups at the highest oral dose tested in rats. Maternal systemic exposure was approximately 5 times the baloxavir exposure in humans at the MRHD.

8.4 Pediatric Use

Treatment of Acute Uncomplicated Influenza in Pediatric Subjects

The safety and effectiveness of XOFLUZA for the treatment of acute uncomplicated influenza in pediatric subjects 12 years of age and older weighing at least 40 kg is supported by one randomized, double-blind, controlled trial in otherwise healthy subjects (Trial 2) and one trial in subjects at high risk of developing influenza-related complications (Trial 3) [see Clinical Studies (14.1)]. A total of 117 otherwise healthy adolescents 12-17 years old were randomized and received either XOFLUZA (N=76) or placebo (N=41) in Trial 2; 38 adolescents aged 12 to 17 years at high risk for influenza complications were randomized and received either XOFLUZA (N=21) or placebo (N=17) in Trial 3. The median time to alleviation of symptoms in influenza-infected adolescent subjects aged 12 to 17 years in Trial 2 was comparable to that observed in adults. In Trial 3, the median time to improvement of symptoms in the limited number of influenza-infected adolescent subjects aged 12 to 17 years was similar in the XOFLUZA and placebo arms [see Clinical Studies (14.1)]. Adverse events reported in adolescents in both trials were similar to those reported in adults [see Adverse Reactions (6.1)].

The safety and efficacy of XOFLUZA in pediatric subjects less than 12 years of age have not been established for the treatment of acute uncomplicated influenza. For information on baloxavir resistance in subjects less than 12 years of age [see Microbiology (12.4)].

Post-Exposure Prophylaxis of Influenza in Pediatric Subjects

The safety and effectiveness of XOFLUZA for post-exposure prophylaxis in adolescents (12 years to < 18 years) is supported by one randomized, double-blind, controlled trial conducted in Japan (Trial 4) [see Clinical Studies (14.3)]. Subjects in this trial were randomized in a 1:1 ratio to receive XOFLUZA or placebo. A total of 12 subjects from ≥ 12 to < 18 years of age received XOFLUZA. The incidence of RT-PCR-confirmed symptomatic influenza was similar in the XOFLUZA and placebo arms in the limited number of adolescent subjects aged 12 to 17 years of age [see Clinical Studies (14.3)]. Adverse events reported in adolescent subjects were similar to those reported in adults in the same trial [see Adverse Reactions (6.1)].

The safety and efficacy of XOFLUZA for post-exposure prophylaxis of influenza in pediatric subjects less than 12 years of age have not been established.

8.5 Geriatric Use

The safety and effectiveness of XOFLUZA in subjects 65 years of age and older has been established and is supported by one randomized, double-blind, controlled trial [see Clinical Studies (14.2)]. In Trial 3, of 730 XOFLUZA-treated subjects at high risk of influenza-related complications, 209 (29%) subjects were 65 years of age and older. The median time to improvement of influenza symptoms in subjects 65 years of age and older was 70 hours in subjects who received XOFLUZA (N=112) and 88 hours in those who received placebo (N=102). The safety profile observed for this population was similar to that reported in the overall trial population except for nausea, which was reported in 6% of elderly subjects compared to 1% of subjects from 18 to 64 years of age.

10 OVERDOSAGE

Treatment of an overdose of XOFLUZA should consist of general supportive measures, including monitoring of vital signs and observation of the clinical status of the patient. There is no specific antidote for overdose with XOFLUZA.

Baloxavir is unlikely to be significantly removed by dialysis due to high serum protein binding [see Clinical Pharmacology (12.3)].

11 DESCRIPTION

XOFLUZA (baloxavir marboxil) is an antiviral PA endonuclease inhibitor.

The active component of XOFLUZA is baloxavir marboxil. The chemical name of baloxavir marboxil is ({(12aR)-12-[(11S)-7,8-Difluoro-6,11-dihydrodibenzo[b,e]thiepin-11-yl]-6,8-dioxo-3,4,6,8,12,12a-hexahydro-1H-[1,4]oxazino[3,4-c]pyrido[2,1-f][1,2,4]triazin-7-yl}oxy)methyl methyl carbonate. The empirical formula of baloxavir marboxil is C27H23F2N3O7S, and the chemical structure is shown below.

Baloxavir marboxil has a molecular mass of 571.55 grams per mole and a partition coefficient (log P) of 2.26. It is freely soluble in dimethylsulfoxide, soluble in acetonitrile, slightly soluble in methanol and ethanol, and practically insoluble in water.

XOFLUZA is supplied as tablets and as granules for oral suspension:

XOFLUZA tablets are white to light yellow, film-coated tablets for oral administration. The inactive ingredients of XOFLUZA tablets are: croscarmellose sodium, hypromellose, lactose monohydrate, microcrystalline cellulose, povidone, sodium stearyl fumarate, talc, and titanium dioxide.

XOFLUZA for oral suspension is supplied as white to light yellow granules in an amber glass bottle. Each bottle contains 40 mg (nominal) of baloxavir marboxil. The granules must be constituted with 20 mL of drinking water or sterile water to yield a 2 mg/mL suspension with strawberry flavor. The inactive ingredients are: colloidal silicon dioxide, hypromellose, maltitol, mannitol, povidone K25, sodium chloride, strawberry flavor, sucralose and talc.

12 CLINICAL PHARMACOLOGY

12.1 Mechanism of Action

Baloxavir marboxil is an antiviral drug with activity against influenza virus [see Microbiology (12.4)].

12.2 Pharmacodynamics

Cardiac Electrophysiology

At twice the expected exposure from recommended dosing, XOFLUZA did not prolong the QTc interval.

Exposure-Response Relationships

When XOFLUZA is dosed by weight, as recommended (40 mg in patients weighing 40–80 kg; 80 mg in patients weighing at least 80 kg), no difference in baloxavir exposure-response (time to alleviation of influenza symptoms in the otherwise healthy population or time to improvement of influenza symptoms in the high risk population) relationship has been observed.

12.3 Pharmacokinetics

Baloxavir marboxil is a prodrug that is almost completely converted to its active metabolite, baloxavir, following oral administration.

Baloxavir pharmacokinetic parameters are presented for healthy adults and adolescents as the mean [% coefficient of variation (%CV)], unless otherwise specified, in Table 4.

Table 4 Pharmacokinetic Parameters of Plasma Baloxavir
Pharmacokinetic Parameters of Plasma Baloxavir in Adults and Adolescents [Trial 2 summary data, mean (%CV)] | XOFLUZA dose 40 mg | XOFLUZA dose 80 mg
AUC (ng∙hr/mL) | 5520 (46.3%) | 6930 (48.6%)
Cmax (ng/mL) | 68.9 (44.9%) | 82.5 (43.0%)
C24 (ng/mL) | 50.9 (45.8%) | 62.6 (45.9%)
C72 (ng/mL) | 24.2 (45.5%) | 30.8 (47.0%)

Table 5 Baloxavir Absorption, Distribution, Metabolism, Elimination Data
Absorption
Tmax (hr) [Median] | 4
Effect of food (relative to fasting) [Meal: approximately 400 to 500 kcal including 150 kcal from fat] | Cmax: ↓48%, AUC0-inf: ↓36%
Distribution
% bound to human serum proteins [in vitro] | 92.9–93.9
Ratio of blood cell to blood | 48.5%–54.4%
Volume of distribution (V/F, L) [Geometric mean (geometric CV%)] | 1180 (20.8%)
Elimination
Clearance (CL/F, L/hr) | 10.3 (22.5%)
Apparent terminal elimination half-life (hr) | 79.1 (22.4%)
Metabolism
Metabolic pathways | Primary: UGT1A3 Secondary: CYP3A4
Excretion
% of dose excreted [Ratio of radioactivity to radio-labeled baloxavir marboxil dose in mass balance study] | Urine: 14.7 (total radioactivity); 3.3 (baloxavir) Feces: 80.1 (total radioactivity)

No clinically significant differences in the pharmacokinetics of baloxavir were observed based on age, sex, creatinine clearance (CrCl: 50 mL/min and above), or moderate hepatic impairment (Child-Pugh class B). The effect of severe renal or hepatic impairment on baloxavir pharmacokinetics has not been evaluated.

Body Weight

Baloxavir exposure decreases as body weight increases. No clinically significant difference in exposure was observed between body weight groups following the approved recommended dosage.

Race/Ethnicity

Based on a population pharmacokinetic analysis, baloxavir exposure is approximately 35% lower in non-Asians as compared to Asians; this difference is not considered clinically significant when the recommended dose was administered.

Drug Interaction Studies

Clinical Studies

No clinically significant changes in the pharmacokinetics of baloxavir marboxil and its active metabolite, baloxavir, were observed when coadministered with itraconazole (combined strong CYP3A and P-gp inhibitor), probenecid (UGT inhibitor), or oseltamivir.

No clinically significant changes in the pharmacokinetics of the following drugs were observed when coadministered with baloxavir marboxil: midazolam (CYP3A4 substrate), digoxin (P-gp substrate), rosuvastatin (BCRP substrate), or oseltamivir.

Animal Studies

Polyvalent Cations: In monkeys, a 48% to 63% decrease in baloxavir exposure was observed when XOFLUZA was coadministered with calcium, aluminum, magnesium, or iron. No study has been conducted in humans.

In Vitro Studies

Cytochrome P450 (CYP) Enzymes: Both baloxavir marboxil and baloxavir do not inhibit CYP1A2, CYP2B6, CYP2C8, CYP2C9, CYP2C19, or CYP2D6 and do not induce CYP1A2, CYP2B6, or CYP3A4.

Uridine diphosphate (UDP)-glucuronosyl transferase (UGT) Enzymes: Both baloxavir marboxil and baloxavir do not inhibit UGT1A1, UGT1A3, UGT1A4, UGT1A6, UGT1A9, UGT2B7, or UGT2B15.

Transporter Systems: Both baloxavir marboxil and baloxavir are substrates of P-glycoprotein (P-gp). Baloxavir does not inhibit organic anion-transporting polypeptides (OATP) 1B1, OATP1B3, organic cation transporter (OCT) 1, OCT2, organic anion transporter (OAT) 1, OAT3, multidrug and toxin extrusion (MATE) 1, or MATE2K.

12.4 Microbiology

Mechanism of Action

Baloxavir marboxil is a prodrug that is converted by hydrolysis to baloxavir, the active form that exerts anti-influenza virus activity. Baloxavir inhibits the endonuclease activity of the polymerase acidic (PA) protein, an influenza virus-specific enzyme in the viral RNA polymerase complex required for viral gene transcription, resulting in inhibition of influenza virus replication. The 50% inhibitory concentration (IC50) values of baloxavir ranged from 1.4 to 3.1 nM (n=4) for influenza A viruses and 4.5 to 8.9 nM (n=3) for influenza B viruses in a PA endonuclease assay. Viruses with reduced susceptibility to baloxavir have amino acid substitutions in the PA protein.

Antiviral Activity

The antiviral activity of baloxavir against laboratory strains and clinical isolates of influenza A and B viruses was determined in an MDCK cell-based plaque reduction assay. The median 50% effective concentration (EC50) values of baloxavir were 0.73 nM (n=31; range: 0.20–1.85 nM) for subtype A/H1N1 strains, 0.83 nM (n=33; range: 0.35–2.63 nM) for subtype A/H3N2 strains, and 5.97 nM (n=30; range: 2.67–14.23 nM) for type B strains. In an MDCK cell-based virus titer reduction assay, the 90% effective concentration (EC90) values of baloxavir against avian subtypes A/H5N1 and A/H7N9 were in the range of 0.80 to 3.16 nM. The relationship between antiviral activity in cell culture and clinical response to treatment in humans has not been established.

Resistance

Cell culture: Influenza A virus isolates with reduced susceptibility to baloxavir were selected by serial passage of virus in cell culture in the presence of increasing concentrations of baloxavir. Reduced susceptibility of influenza A virus to baloxavir was conferred by amino acid substitutions I38T (A/H1N1 and A/H3N2) and E199G (A/H3N2) in the PA protein of the viral RNA polymerase complex.

Clinical studies: Influenza A and B viruses with treatment-emergent amino acid substitutions at positions associated with reduced susceptibility to baloxavir in cell culture were observed in clinical studies (Table 6). In adult and adolescent subjects who had a confirmed influenza virus infection, the overall frequencies of treatment-emergent amino acid substitutions associated with reduced susceptibility to baloxavir were 4.5% (6/134), 10.9% (53/485), and 0.9% (2/224) in influenza A/H1N1, A/H3N2, and B virus infections, respectively, in pooled data from Trials 1, 2, and 3 [see Clinical Studies (14)]. In Trial 4, of 374 subjects, including 71 subjects <12 years of age, who received XOFLUZA post-exposure prophylaxis, 49 were viral RNA-positive post-baseline, including 31 subjects who were evaluated for resistance. Of these 31 subjects, influenza virus with substitutions associated with reduced susceptibility to baloxavir was identified in 7/7 subjects who developed clinical influenza (as described for the primary endpoint) and 8/24 other subjects evaluated who did not meet the primary endpoint definition for clinical influenza [see Clinical Studies (14)]. Selection of influenza viruses with reduced susceptibility to baloxavir has occurred at higher frequencies in pediatric subjects, and such viruses were detected with overall frequencies of 20% (4/20), 27.9% (34/122), and 0% (0/21) in influenza A/H1N1, A/H3N2, and B virus infections, respectively, in pooled data from 3 pediatric treatment trials in subjects <12 years of age.

Table 6 Treatment-Emergent Amino Acid Substitutions in PA Associated with Reduced Susceptibility to Baloxavir
Influenza Type/Subtype | A/H1N1 | A/H3N2 | B
Amino Acid Substitution | E23K/R, I38F/N/S/T | E23G/K, A37T, I38M/T, E199G | I38T

None of the treatment-emergent substitutions associated with reduced susceptibility to baloxavir were identified in virus from pretreatment respiratory specimens in the clinical studies. Strains containing substitutions known to be associated with reduced susceptibility to baloxavir were identified in approximately 0.05% of PA sequences in the National Center for Biotechnology Information/GenBank database (queried August 2018).

Prescribers should consider currently available surveillance information on influenza virus drug susceptibility patterns and treatment effects when deciding whether to use XOFLUZA.

Cross-Resistance

Cross-resistance between baloxavir and neuraminidase (NA) inhibitors, or between baloxavir and M2 proton pump inhibitors (adamantanes), is not expected because these drugs target different viral proteins. Baloxavir is active against NA inhibitor-resistant strains, including A/H1N1 and A/H5N1 viruses with the NA substitution H275Y (A/H1N1 numbering), A/H3N2 virus with the NA substitutions E119V or R292K, A/H7N9 virus with the NA substitution R292K (A/H3N2 numbering), and type B virus with the NA substitutions R152K or D198E (A/H3N2 numbering). The NA inhibitor oseltamivir is active against viruses with reduced susceptibility to baloxavir, including A/H1N1 virus with PA substitutions E23K or I38F/T, A/H3N2 virus with PA substitutions E23G/K, A37T, I38M/T, or E199G, and type B virus with the PA substitution I38T. Influenza virus may carry amino acid substitutions in PA that reduce susceptibility to baloxavir and at the same time carry resistance-associated substitutions for NA inhibitors and M2 proton pump inhibitors. The clinical relevance of phenotypic cross-resistance evaluations has not been established.

Immune Response

Interaction studies with influenza vaccines and baloxavir marboxil have not been conducted.

13 NONCLINICAL TOXICOLOGY

13.1 Carcinogenesis, Mutagenesis, Impairment of Fertility

Carcinogenesis

Carcinogenicity studies have not been performed with baloxavir marboxil.

Mutagenesis

Baloxavir marboxil and the active metabolite, baloxavir, were not mutagenic in in vitro and in in vivo genotoxicity assays, which included bacterial mutation assays in S. typhimurium and E. coli, micronucleus tests with cultured mammalian cells, and in the rodent micronucleus assay.

Impairment of Fertility

In a fertility and early embryonic development study in rats, doses of baloxavir marboxil at 20, 200, or 1,000 mg/kg/day were administered to females for 2 weeks before mating, during mating, and until day 7 of pregnancy. Males were dosed for 4 weeks before mating and throughout mating. There were no effects on fertility, mating performance, or early embryonic development at any dose level, resulting in systemic drug exposure (AUC) approximately 5 times the MRHD.

14 CLINICAL STUDIES

14.1 Treatment of Acute Uncomplicated Influenza—Otherwise Healthy Subjects

Adults and Adolescents (Aged 12 Years and Older)

Two randomized, controlled, double-blinded clinical trials conducted in two different influenza seasons evaluated efficacy and safety of XOFLUZA in otherwise healthy subjects with acute uncomplicated influenza.

In Trial 1, a placebo-controlled phase 2 dose-finding trial, a single oral dose of XOFLUZA was compared with placebo in 400 adult subjects 20 to 64 years of age in Japan. All subjects in Trial 1 were Asian, the majority of subjects were male (62%), and the mean age was 38 years. In this trial, among subjects who received XOFLUZA and had influenza virus typed, influenza A/H1N1 was the predominant strain (63%), followed by influenza B (25%), and influenza A/H3N2 (12%).

In Trial 2 (NCT02954354), a phase 3, randomized, double-blind, active- and placebo-controlled trial, XOFLUZA was studied in 1,436 otherwise healthy adults and adolescents with signs and symptoms of influenza in the U.S. and Japan. Subjects were 12 to 64 years of age and weighed at least 40 kg. Adults ages 20 to 64 years received weight-based XOFLUZA (subjects who weighed 40 to less than 80 kg received 40 mg and subjects who weighed 80 kg and above received 80 mg) (N=612) or placebo as a single oral dose on day 1 (N=310) or oseltamivir twice a day for 5 days (N=514). Subjects in the XOFLUZA and placebo arms received a placebo for the duration of oseltamivir dosing after XOFLUZA or placebo dosing in that arm. Adolescent subjects 12 to less than 20 years of age received weight-based XOFLUZA or placebo as a single oral dose.

Seventy-eight percent of subjects in Trial 2 were Asian, 17% were White, and 4% were Black or African American. The mean age was 34 years, and 11% of subjects were less than 20 years of age; 54% of subjects were male and 46% female. In Trial 2, 1,062 of 1,436 enrolled subjects had influenza confirmed by RT-PCR and were included in the efficacy analysis (XOFLUZA N=455, placebo N=230, or oseltamivir N=377). Among subjects who received XOFLUZA and had influenza virus typed, influenza A/H3N2 was the predominant strain (90%), followed by influenza B (9%), and influenza A/H1N1 (2%).

In both Trials 1 and 2, eligible subjects had an axillary temperature of at least 38˚C, at least one moderate or severe respiratory symptom (cough, nasal congestion, or sore throat), and at least one moderate or severe systemic symptom (headache, feverishness or chills, muscle or joint pain, or fatigue), and all were treated within 48 hours of symptom onset. Subjects participating in the trial were required to self-assess their influenza symptoms as "none," "mild," "moderate," or "severe" twice daily. The primary efficacy population was defined as those with a positive rapid influenza diagnostic test (Trial 1) or positive influenza reverse transcription polymerase chain reaction (RT-PCR) (Trial 2) at trial entry.

The primary endpoint of both trials, time to alleviation of symptoms, was defined as the time when all seven symptoms (cough, sore throat, nasal congestion, headache, feverishness, myalgia, and fatigue) had been assessed by the subject as none or mild for a duration of at least 21.5 hours.

In both trials, XOFLUZA treatment at the recommended dose resulted in a statistically significant shorter time to alleviation of symptoms compared with placebo in the primary efficacy population (Tables 7 and 8).

Table 7 Time to Alleviation of Symptoms After Single Dose in Otherwise Healthy Adults with Acute Uncomplicated Influenza in Trial 1 (Median Hours)
 | XOFLUZA 40 mg (95% CI [CI: Confidence interval]) N=100 | Placebo (95% CI) N=100
Adults (20 to 64 Years of Age) | 50 hours [XOFLUZA treatment resulted in a statistically significant shorter time to alleviation of symptoms compared to placebo using the Gehan-Breslow's generalized Wilcoxon test (p-value: 0.014, adjusted for multiplicity using the Bonferroni method). The primary analysis using the Cox Proportional Hazards Model did not reach statistical significance (p-value: 0.165).] (45, 64) | 78 hours (68, 89)

Table 8 Time to Alleviation of Symptoms After Single Dose in Otherwise Healthy Subjects 12 Years of Age and Older with Acute Uncomplicated Influenza in Trial 2 (Median Hours)
 | XOFLUZA 40 mg or 80 mg (95% CI [CI: Confidence interval]) N=455 | Placebo (95% CI) N=230
Subjects (≥ 12 Years of Age) | 54 hours [XOFLUZA treatment resulted in a statistically significant shorter time to alleviation of symptoms compared to placebo using the Peto-Prentice's generalized Wilcoxon test (p-value: < 0.001).] (50, 59) | 80 hours (73, 87)

In Trial 2, there was no difference in the time to alleviation of symptoms between subjects (age ≥ 20 years) who received XOFLUZA (54 hours) and those who received oseltamivir (54 hours). For adolescent subjects (12 to 17 years of age) in Trial 2, the median time to alleviation of symptoms for subjects infected with influenza and who received XOFLUZA (N=63) was 54 hours (95% CI of 43, 81) compared to 93 hours (95% CI of 64, 118) in the placebo arm (N=27).

The number of subjects who received XOFLUZA at the recommended dose and who were infected with influenza type B virus was limited, including 24 subjects in Trial 1 and 38 subjects in Trial 2. In the influenza B subset in Trial 1, the median time to alleviation of symptoms in subjects who received 40 mg XOFLUZA was 63 hours (95% CI of 43, 70) compared to 83 hours (95% CI of 58, 93) in subjects who received placebo. In the influenza B subset in Trial 2, the median time to alleviation of symptoms in subjects who received 40 mg or 80 mg XOFLUZA was 93 hours (95% CI of 53, 135) compared to 77 hours (95% CI of 47, 189) in subjects who received placebo.

14.2 Treatment of Acute Uncomplicated Influenza—High Risk Subjects

Trial 3 (NCT02949011) was a randomized, double-blind, placebo- and active-controlled trial to evaluate the efficacy and safety of a single oral dose of XOFLUZA compared with placebo or oseltamivir in adult and adolescent subjects 12 years of age or older with influenza who were at high risk of developing influenza-related complications.

A total of 2,182 subjects with signs and symptoms of influenza were randomized to receive a single oral dose of 40 mg or 80 mg of XOFLUZA according to body weight (subjects who weighed 40 to less than 80 kg received 40 mg and subjects who weighed 80 kg and above received 80 mg) (N=729), oseltamivir 75 mg twice daily for 5 days (N=725), or placebo (N=728). Twenty-eight percent of subjects were Asian, 59% were White, and 10% were Black or African American. The mean age was 52 years, and 3% of subjects were less than 18 years of age; 43% of subjects were male and 57% female.

High risk factors were based on the Centers for Disease Control and Prevention definition^1 of health factors known to increase the risk of developing serious complications from influenza. The majority of subjects had underlying asthma or chronic lung disease, diabetes, heart disease, morbid obesity, or were 65 years of age or older.

In Trial 3, 1,158 of the 2,182 enrolled subjects had influenza confirmed by RT-PCR and were included in the efficacy analysis (XOFLUZA N=385, placebo N=385, or oseltamivir N=388). Among subjects in whom only one type/subtype of influenza virus was identified, 50% were infected with subtype A/H3N2, 43% were infected with type B, and 7% were infected with subtype A/H1N1.

Eligible subjects had an axillary temperature of at least 38°C, at least one moderate or severe respiratory symptom (cough, nasal congestion, or sore throat), and at least one moderate or severe systemic symptom (headache, feverishness or chills, muscle or joint pain, or fatigue), and all were treated within 48 hours of symptom onset. Subjects participating in the trial were required to self-assess their influenza symptoms as "none," "mild," "moderate," or "severe" twice daily. A total of 215 subjects (19%) had preexisting symptoms (cough, muscle or joint pain, or fatigue) associated with their underlying high risk condition that were worsened due to influenza infection. The primary efficacy endpoint was time to improvement of influenza symptoms (cough, sore throat, headache, nasal congestion, feverishness or chills, muscle or joint pain, and fatigue). This endpoint included alleviation of new symptoms and improvement of any preexisting symptoms that had worsened due to influenza. A statistically significant improvement in the primary endpoint was observed for XOFLUZA when compared with placebo (see Table 9).

Table 9 Time to Improvement of Symptoms After Single Dose in High Risk Subjects 12 Years of Age and Older with Acute Uncomplicated Influenza in Trial 3 (Median Hours)
XOFLUZA 40 mg or 80 mg [The dosage of XOFLUZA was based on subject's weight.] (95% CI [CI: Confidence interval]) N=385 | Placebo (95% CI) N=385
73 hours [XOFLUZA treatment resulted in a significant reduction in Time to Improvement of Influenza Symptoms compared to placebo using Peto-Prentice's generalized Wilcoxon test (p-value: < 0.001).] (67, 85) | 102 hours (93, 113)

There was no statistically significant difference in the median time to improvement of influenza symptoms in the subjects who received XOFLUZA (73 hours) and those who received oseltamivir (81 hours). The median time to improvement of influenza symptoms in the limited number of adolescent subjects aged 12 to 17 years infected with influenza virus was similar for subjects who received XOFLUZA (188 hours) or placebo (191 hours) (N=13 and N=12, respectively).

For subjects infected with type B virus, the median time to improvement of influenza symptoms was 75 hours in the XOFLUZA group (95% CI of 67, 90) compared to 101 hours in the placebo group (95% CI of 83, 116).

14.3 Post-Exposure Prophylaxis of Influenza

Trial 4 was a phase 3, randomized, double-blind, multicenter, placebo-controlled study designed to evaluate the efficacy of a single oral dose of XOFLUZA compared with placebo in the prevention of influenza in subjects who were household contacts of influenza-infected patients in Japan. Influenza-infected index patients were required to have onset of symptoms for ≤ 48 hours, and subjects (household contacts) were required to have lived with the influenza-infected index patient for ≥ 48 hours.

A total of 607 subjects (XOFLUZA N=303, placebo N=304) ≥ 12 years of age were randomized and received a single oral dose of XOFLUZA according to body weight and age, or placebo, on day 1. Subjects received 40 mg or 80 mg of XOFLUZA according to body weight (40 to < 80 kg or ≥ 80 kg, respectively). The primary efficacy endpoint was the proportion of household subjects who were infected with influenza virus and presented with fever and at least one respiratory symptom from day 1 to day 10. Influenza infection was confirmed by RT-PCR, fever was defined as a body temperature (axillary) ≥ 37.5°C, and respiratory symptoms were defined as having a symptom of "cough" or "nasal discharge/nasal congestion" with a severity of moderate or severe as assessed by the subject.

The mean age of subjects that were ≥ 12 years of age in Trial 4 was 40 years; 33 (5%) were ≥ 12 to < 18 years of age, 551 (91%) were ≥ 18 to < 65 years of age, and 23 (4%) were ≥ 65 years of age. All subjects were Asian, 84% were female, and 16% were male. The predominant influenza virus strains in the index patients of this study were the A/H3N2 subtype (49%) and the A/H1N1 subtype (46%), followed by the B subtype (1%).

In subjects that were ≥12 years of age, there was a statistically significant reduction in the proportion of household contacts (subjects) with laboratory-confirmed clinical influenza from 13% in the placebo group to 1% in the XOFLUZA group (see Table 10).

Table 10 Proportion of Household Contacts (Subjects 12 Years of Age and Older) Infected with Influenza Virus with Fever and at Least One Respiratory Symptom (Trial 4)
XOFLUZA (95% CI [CI: Confidence interval XOFLUZA treatment resulted in a significant reduction in the risk ratio of patients who were infected with influenza virus and presented with fever compared to placebo using modified Poisson regression for a binary response (p-value: < 0.0001).]) N=303 | Placebo (95% CI) N=304
1% (0, 3) | 13% (10, 17)

15 REFERENCES

1. "People at High Risk For Flu Complications." CDC. https://www.cdc.gov/flu/highrisk/index.htm.

16 HOW SUPPLIED/STORAGE AND HANDLING

Product: 50090-4102

NDC: 50090-4102-0 2 TABLET, FILM COATED in a BLISTER PACK / 1 in a CARTON

17 PATIENT COUNSELING INFORMATION

Advise the patient to read the FDA-approved patient labeling (Patient Information).

Important Dosing Information

Instruct patients to begin treatment with XOFLUZA as soon as possible at the first appearance of influenza symptoms, within 48 hours of onset of symptoms. Instruct patients to start taking XOFLUZA for prevention as soon as possible after exposure [see Dosage and Administration (2)].

XOFLUZA can be taken with or without food, but advise patients not to take with dairy products, calcium-fortified beverages, polyvalent cation-containing laxatives, antacids, or oral supplements (e.g., calcium, iron, magnesium, selenium, or zinc) [see Dosage and Administration (2) and Drug Interactions (7.1)].

Advise patients to follow the healthcare provider's dosing recommendation for a single, one-time dose of XOFLUZA. XOFLUZA is dosed based on weight and is available in tablet form or as for oral suspension for oral or enteral use.

Tablets: Provided as a blister card containing either one tablet of 40 mg, or one tablet of 80 mg as a single dose [see Dosage and Administration (2.2)].

For oral suspension: Provided in a bottle containing 40 mg/20 mL (2 mg/mL) after constitution by the healthcare provider [see How Supplied/Storage and Handling (16)]. The total prescribed dose of XOFLUZA for oral suspension may require more than one bottle. The suspension should be taken as soon as possible but no later than 10 hours after constitution by the healthcare provider because the product does not contain a preservative [see Dosage and Administration (2.3)].

Hypersensitivity

Advise patients and/or caregivers of the risk of severe allergic reactions such as anaphylaxis, angioedema, urticaria, and erythema multiforme. Instruct patients and/or caregivers to seek immediate medical attention if an allergic-like reaction occurs or is suspected [see Contraindications (4) and Warnings and Precautions (5.1)].

Influenza Vaccines

Because of the potential for antivirals to decrease the effectiveness of live attenuated influenza vaccines, advise patients to consult their healthcare provider prior to receiving a live attenuated influenza vaccine after taking XOFLUZA [see Drug Interactions (7.2)].

Distributed by:
Genentech USA, Inc.
A Member of the Roche Group
1 DNA Way
South San Francisco, CA 94080-4990

XOFLUZA® is a registered trademark of Genentech, Inc.
© 2021 Genentech USA, Inc.

PATIENT INFORMATION

XOFLUZA® (zoh-FLEW-zuh)
(baloxavir marboxil)
tablets

XOFLUZA® (zoh-FLEW-zuh)
(baloxavir marboxil)
for oral suspension

What is XOFLUZA?
XOFLUZA is a prescription medicine used to:

- treat the flu (influenza) in people 12 years of age and older who have had flu symptoms for no more than 48 hours.
- prevent the flu in people 12 years of age and older following contact with a person who has the flu.

It is not known if XOFLUZA is safe and effective in children less than 12 years of age.
XOFLUZA does not treat or prevent illness that is caused by infections other than the influenza virus.
XOFLUZA does not prevent bacterial infections that may happen with the flu.

Do not take XOFLUZA if you are allergic to baloxavir marboxil or any of the ingredients in XOFLUZA. See the end of this leaflet for a complete list of ingredients in XOFLUZA.

Before you take XOFLUZA, tell your healthcare provider about all of your medical conditions, including if you:

- are pregnant or plan to become pregnant. It is not known if XOFLUZA can harm your unborn baby.
- are breastfeeding or plan to breastfeed. It is not known if XOFLUZA passes into your breast milk.

Tell your healthcare provider about all the medicines you take, including prescription and over-the-counter medicines, vitamins, and herbal supplements.
Talk to your healthcare provider before you receive a live flu vaccine after taking XOFLUZA.
Know the medicines you take. Keep a list of them to show your healthcare provider and pharmacist when you get a new medicine.

How should I take XOFLUZA?

- Take XOFLUZA exactly as directed by your healthcare provider or pharmacist.
- Your healthcare provider will either prescribe:
  - XOFLUZA tablet as a single one-time dose, or
  - XOFLUZA oral suspension provided with a measuring device (an oral syringe or measuring cup) to be given as a single one-time dose.
- XOFLUZA may be given through a feeding tube. Follow your healthcare provider's instructions for giving XOFLUZA through a feeding tube.
- Take XOFLUZA with or without food.
- Do not take XOFLUZA with dairy products, calcium-fortified beverages, laxatives, antacids or oral supplements containing iron, zinc, selenium, calcium or magnesium.
- If you take too much XOFLUZA, go to the nearest emergency room right away.

If you are taking XOFLUZA for oral suspension:

- The pharmacist will mix XOFLUZA for oral suspension before it is given to you. If XOFLUZA is not given to you as a liquid or measuring device was not provided, contact your pharmacist.
- Take XOFLUZA before the expiration time and date written by the pharmacist on the bottle label. Do not take XOFLUZA if the expiration time and date have passed. Throw away (discard) the bottle and contact your healthcare provider.
- The total prescribed dose of XOFLUZA for oral suspension may require more than one bottle of XOFLUZA.

Giving a dose of XOFLUZA for oral suspension:
Step 1. Swirl the XOFLUZA for oral suspension bottle well before each use. Do not shake.
Step 2. Open the bottle by pushing downward on the child resistant bottle cap and twisting it in the direction of the arrow.
Step 3. Measure the oral suspension with the measuring device provided by the pharmacist to be sure you give the prescribed dose.
Step 4. The patient should sit in an upright position when taking XOFLUZA.

- Do not give XOFLUZA while the patient is lying down.
- Do not mix XOFLUZA with soft food or another liquid to give the medicine.

Step 5. Give the full contents of the measuring device. You may need more than one bottle for your prescribed dose.
Step 6. Close the bottle. Throw away any remaining oral suspension and the measuring device.

What are the possible side effects of XOFLUZA?
XOFLUZA may cause serious side effects, including:

- Allergic reactions. Get emergency medical help right away if you develop any of these signs or symptoms of an allergic reaction:

- trouble breathing
- skin rash, hives or blisters

- swelling of your face, throat or mouth
- dizziness or lightheadedness

The most common side effects of XOFLUZA for treatment of the flu in adults and adolescents include:

- diarrhea
- bronchitis
- nausea

- sinusitis
- headache

XOFLUZA is not effective in treating or preventing infections other than influenza. Other kinds of infections can appear like flu or occur along with flu and may need different kinds of treatment.
Tell your healthcare provider if you feel worse or develop new symptoms during or after treatment with XOFLUZA or if your flu symptoms do not start to get better.
These are not all the possible side effects of XOFLUZA.
Call your doctor for medical advice about side effects. You may report side effects to FDA at 1-800-FDA-1088.

How should I store XOFLUZA?
XOFLUZA tablets:

- Store XOFLUZA tablet at room temperature between 68°F to 77°F (20°C to 25°C).
- Store XOFLUZA tablet in the blister package that it comes in.

XOFLUZA for oral suspension:

- Store XOFLUZA for oral suspension at room temperature between 68°F to 77°F (20°C to 25°C).
- Keep XOFLUZA for oral suspension in the original container. Use by the expiration time and date written on bottle label.
- Throw away any XOFLUZA for oral suspension not used by the time and date on the bottle label.

Keep XOFLUZA and all medicines out of the reach of children.

General information about the safe and effective use of XOFLUZA.
Medicines are sometimes prescribed for purposes other than those listed in a Patient Information leaflet. Do not use XOFLUZA for a condition for which it was not prescribed. Do not give XOFLUZA to other people, even if they have the same symptoms that you have. It may harm them. You can ask for information about XOFLUZA that is written for health professionals.

What are the ingredients in XOFLUZA?
Active ingredient: baloxavir marboxil
XOFLUZA tablets inactive ingredients: croscarmellose sodium, hypromellose, lactose monohydrate, microcrystalline cellulose, povidone, sodium stearyl fumarate, talc, and titanium dioxide.
XOFLUZA for oral suspension inactive ingredients: colloidal silicon dioxide, hypromellose, maltitol, mannitol, povidone K25, sodium chloride, strawberry flavor, sucralose and talc.
Distributed by: Genentech USA, Inc., A Member of the Roche Group, 1 DNA Way, South San Francisco, CA 94080-4990
XOFLUZA® is a registered trademark of Genentech, Inc. © 2021 Genentech USA, Inc.
For more information, go to www.XOFLUZA.com or call 1-855-XOFLUZA (1-855-963-5892).

This Patient Information has been approved by the U.S. Food and Drug Administration.

Revised: 3/2021

Representative sample of labeling (see the HOW SUPPLIED section for complete listing):